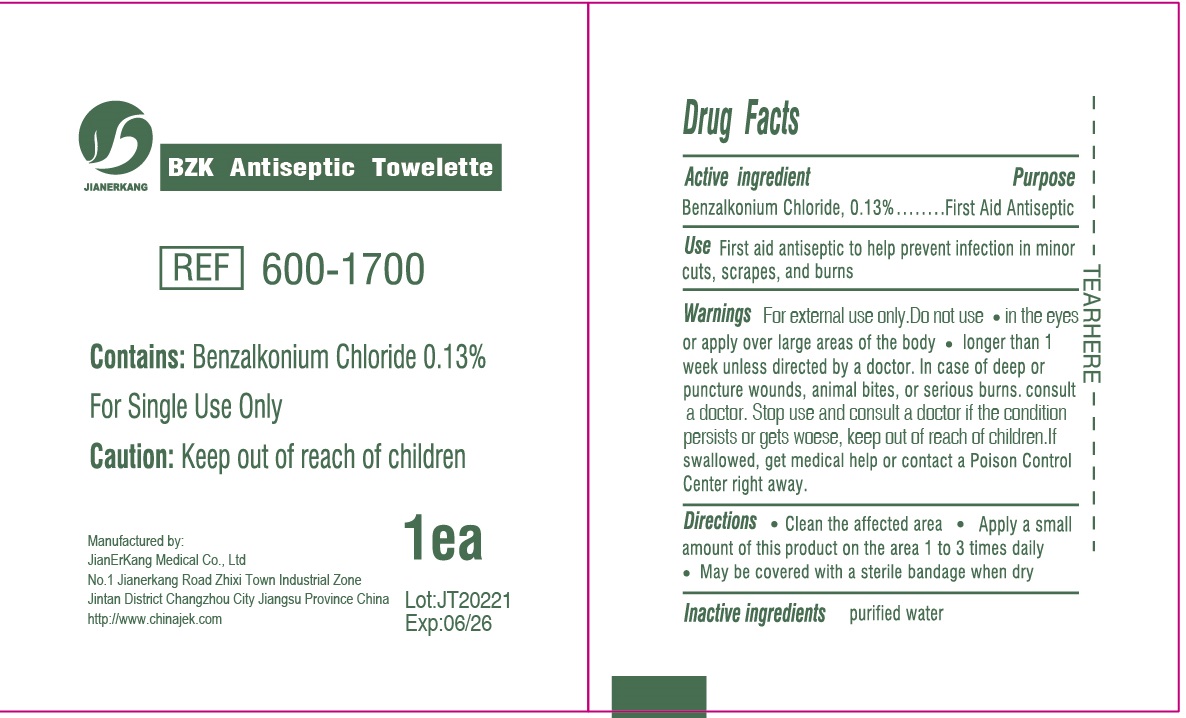 DRUG LABEL: BZK Antiseptic Towelette Non-Sterile
NDC: 34645-0017 | Form: CLOTH
Manufacturer: Jianerkang Medical Co., Ltd
Category: otc | Type: HUMAN OTC DRUG LABEL
Date: 20231023

ACTIVE INGREDIENTS: BENZALKONIUM CHLORIDE 1.3 mg/1 g
INACTIVE INGREDIENTS: WATER

BZK Antiseptic Towelette Non-Sterile

Active ingredient

Benzalkonium Chloride, 0.13%

Purpose

First Aid Antiseptic

Use

First aid antiseptic to help prevent infection in minor cuts, scrapes, and burns

Warnings

- For external use only.

Do not use

- in the eyes or apply over large areas of the body
- longer than 1 week unless directed by a doctor. In case of deep or puncture wounds, animal bites, or serious burns. consult a doctor.

Stop use and consult a doctor

if the condition persists or gets woese,

Keep out of reach of children.

If swallowed, get medical help or contact a Poison Control Center right away.

Directions

- Clean the affected area
- Apply a small amount of this product on the area 1 to 3 times daily.
- May be covered with a sterile bandage when dry

Inactive ingredients

purified water